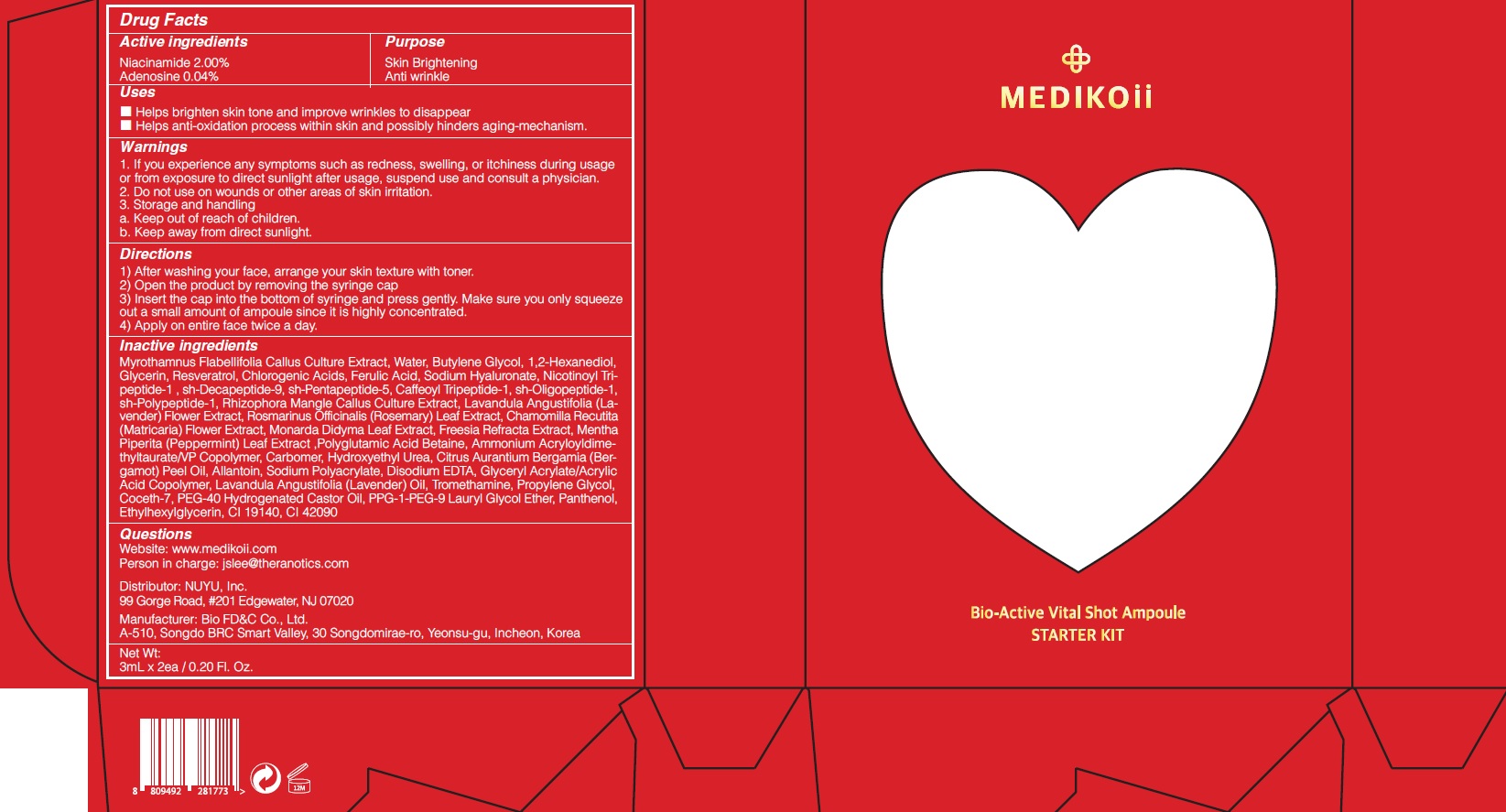 DRUG LABEL: MEDIKOii Bio Active Vital Shot Ampoule Starter Kit
NDC: 72695-0010 | Form: GEL
Manufacturer: THERANOTICS CO.,LTD.
Category: otc | Type: HUMAN OTC DRUG LABEL
Date: 20200529

ACTIVE INGREDIENTS: Niacinamide 2 g/100 mL; ADENOSINE 0.04 g/100 mL
INACTIVE INGREDIENTS: Water; Butylene Glycol

Drug Facts

ACTIVE INGREDIENTS

Niacinamide 2.00%
Adenosine 0.04%

INACTIVE INGREDIENTS

Myrothamnus Flabellifolia Callus Culture Extract, Water, Butylene Glycol, 1,2-Hexanediol, Glycerin, Resveratrol, Chlorogenic Acids, Ferulic Acid,
Sodium Hyaluronate, Nicotinoyl Tripeptide-1 , sh-Decapeptide-9, sh-Pentapeptide-5, Caffeoyl Tripeptide-1, sh-Oligopeptide-1, sh-Polypeptide-1,
Rhizophora Mangle Callus Culture Extract, Lavandula Angustifolia (Lavender) Flower Extract, Rosmarinus Officinalis (Rosemary) Leaf Extract, Chamomilla Recutita (Matricaria) Flower Extract, Monarda Didyma Leaf Extract, Freesia Refracta Extract, Mentha Piperita (Peppermint) Leaf Extract ,Polyglutamic Acid, Betaine, Ammonium Acryloyldimethyltaurate/VP Copolymer, Carbomer,, Hydroxyethyl Urea, Citrus Aurantium Bergamia (Bergamot) Peel Oil, Allantoin, Sodium Polyacrylate, Disodium EDTA, Glyceryl Acrylate/Acrylic Acid Copolymer, Lavandula Angustifolia (Lavender) Oil, Tromethamine, Propylene Glycol, Coceth-7, PEG-40 Hydrogenated Castor Oil, PPG-1-PEG-9 Lauryl Glycol Ether, Panthenol, Ethylhexylglycerin, CI 19140, CI 42090

PURPOSE

Skin Brightening
Anti wrinkle

WARNINGS

1.If you experience any symptoms such as redness, swelling, or itchiness during usage or from exposure to direct sunlight after usage, suspend use and consult a physician.
2. Do not use on wounds or other areas of skin irritation.
3. Storage and handling
a. Keep out of reach of children.
b. Keep away from direct sunlight.

KEEP OUT OF REACH OF CHILDREN

Uses

■ Helps brighten skin tone and improve wrinkles to disappear
■ Helps anti-oxidation process within skin and possibly hinders aging-mechanism.

Directions

1) After washing your face, arrange your skin texture with toner.
2) Open the product by removing the syringe cap
3) Insert the cap into the bottom of syringe and press gently. Make sure you only squeeze out a small amount of ampoule since it is highly concentrated.
4) Apply on entire face twice a day.

QUESTIONS

Website: www.medikoii.com
Person in charge: jslee@theranotics.com